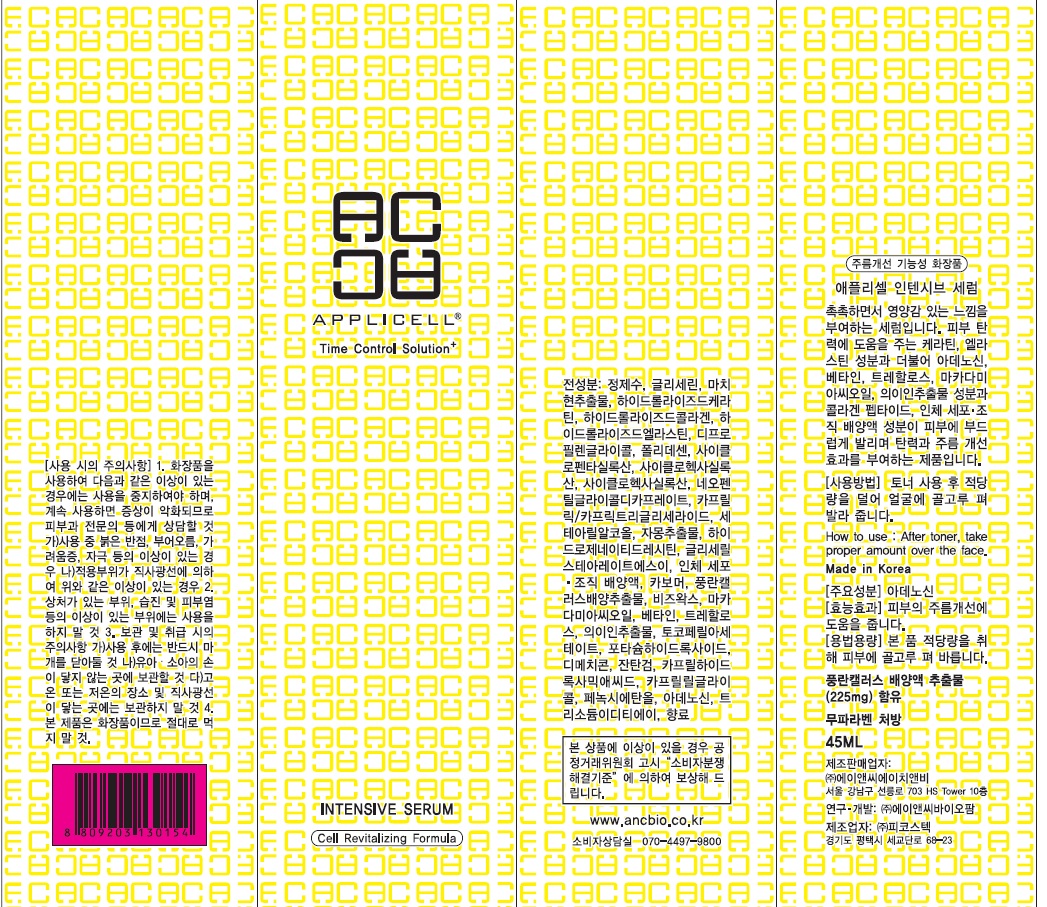 DRUG LABEL: Applicell Intensive Serum
NDC: 71098-030 | Form: CREAM
Manufacturer: Anc HnB Inc.
Category: otc | Type: HUMAN OTC DRUG LABEL
Date: 20161125

ACTIVE INGREDIENTS: Adenosine 0.01 g/45 mL
INACTIVE INGREDIENTS: Water; Glycerin

ACTIVE INGREDIENT

Active Ingredient: Adenosine 0.04%

INACTIVE INGREDIENT

Inactive Ingredients: Water, Glycerin, Portulaca Oleracea Extract, Hydrolyzed Keratin, Hydrolyzed Collagen, Hydrolyzed Elastin, Dipropylene Glycol, Hydrogenated Polydecene, Cyclopentasiloxane, Cyclohexasiloxane, Neopentyl Glycol Dicaprate, Caprylic/Capric Triglyceride, Cetearyl Alcohol, Citrus Paradisi (Grapefruit) Fruit Extract, Hydrogenated Lecithin, Glyceryl Stearate SE, Human fibroblast Conditioned Media, Carbomer, Neofinetia Falcata Callus Culture Extract, Beeswax, Macadamia Ternifolia Seed Oil, Betaine, Trehalose, Coix Lacryma-Jobi Ma-yuen Seed Extract, Tocopheryl Acetate, Potassium Hydroxide, Dimethicone, Xanthan Gum, Caprylhydroxamic Acid, Caprylyl Glycol, Phenoxyethanol, Trisodium EDTA, Fragrance

PURPOSE

Purpose: Skin Protectant

WARNINGS

Warnings: For external use only When using this product do not get into eyes, Stop use and ask a doctor if rash occurs Do not use on - deep puncture wounds - animal bites - serious burns Keep out of reach of children

KEEP OUT OF REACH OF CHILDREN

INDICATIONS & USAGE

Indications & usage: APPLICELL Intensive Serum enhances skin elasticity and improves skin wrinkle.

DOSAGE & ADMINISTRATION

How to use: After toner, take proper amount over the face.